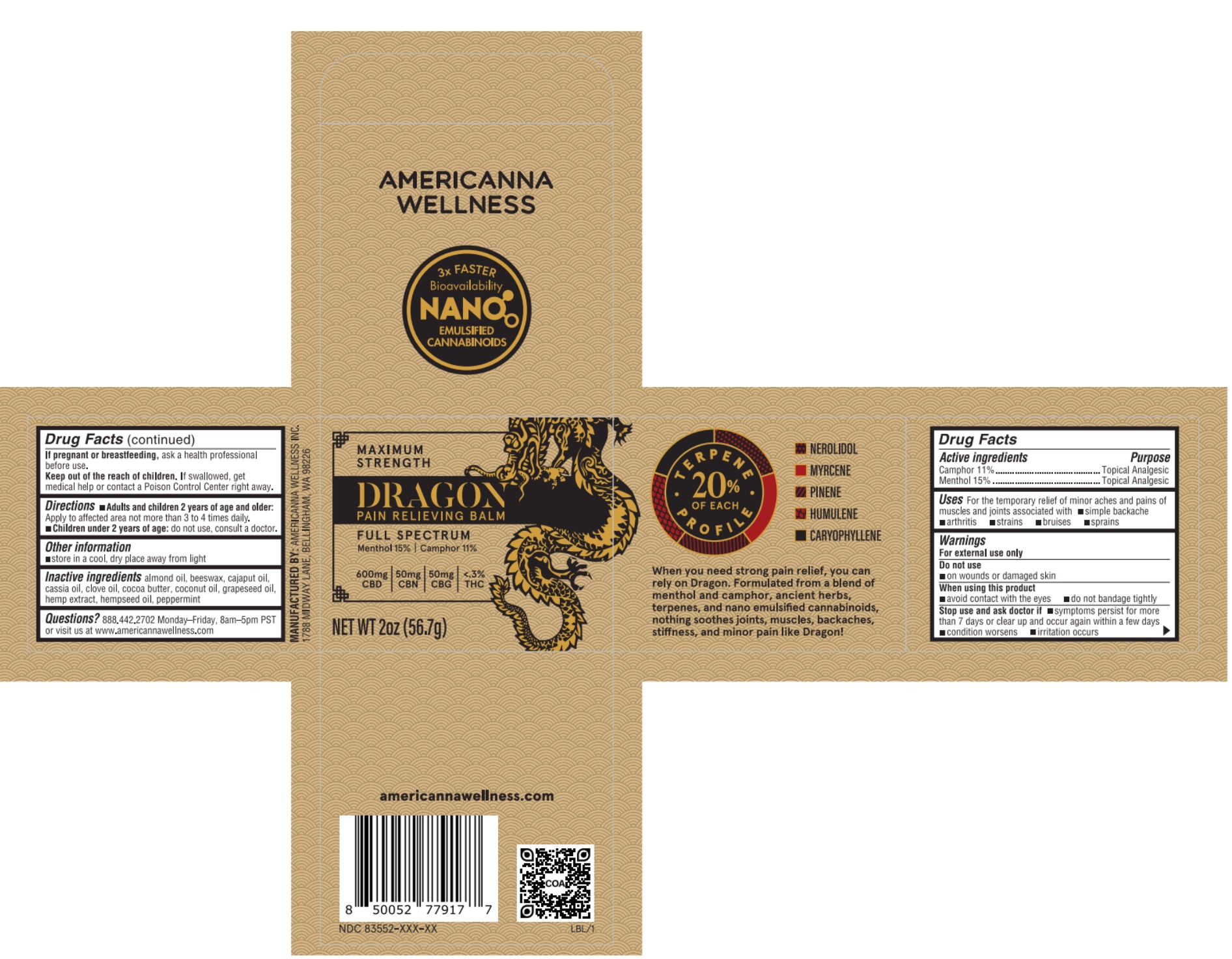 DRUG LABEL: Dragon Pain Relieving Balm
NDC: 83552-123 | Form: SALVE
Manufacturer: Americanna Wellness, Inc.
Category: otc | Type: HUMAN OTC DRUG LABEL
Date: 20251112

ACTIVE INGREDIENTS: CAMPHOR (NATURAL) 11 g/100 g; MENTHOL 15 g/100 g
INACTIVE INGREDIENTS: CAJUPUT OIL; GRAPE SEED OIL; CANNABIS SATIVA SEED OIL; CLOVE OIL; CHINESE CINNAMON OIL; COCONUT OIL; YELLOW WAX; HEMP; ALMOND OIL; COCOA BUTTER; PEPPERMINT

Active ingredients

Camphor 11%

Menthol 15%

Purpose

Camphor 11%.....................Topical Analgesic

Menthol 15%.......................Topical Analgesic

Uses

For the temporary relief of minor achse and pains of muscles and joints associated with

- simple backache
- arthritis
- strains
- bruises
- sprains

Warnings

For external use only

Do not use

- on wounds or damaged skin

When using this product

- avoid contact with the eyes
- do not bandage tightly

Stop use and ask doctor if

- symptoms persist for more than 7 days or clear up and occur again within a few days
- condition worsens
- irritation occurs

PREGNANCY OR BREAST FEEDING

If pregnant or breastfeeding,ask a health professional before use.

Keep out of reach of children.If swallowed, get medical help or contact a Poison Control Center right away.

Directions

- Adults and children 2 years of age and older:Apply to affected area not more than 3 to 4 times daily.
- Children under 2 years of age:do not use, consult a doctor.

Other information

- store in a cool, dry place away from light

Inactive ingredients

almond oil, beeswax, cajaput oil, cassia oil, clove oil, cocoa butter, coconut oil, grapeseed oil, hemp extract, hempseed oil, peppermint

Questions?

888.442.2702 Monday-Friday, 8am-5pm PST or visit us at www.americannawellness.com

PACKAGE LABEL

Maximum Strength

Dragon Pain Relieving Balm

Full Spectrum

Menthol 15% | Camphor 11%

600mg CBD

50mg CBN

50mg CBG

<.3% THC

Net Wt 2oz (56.7g)